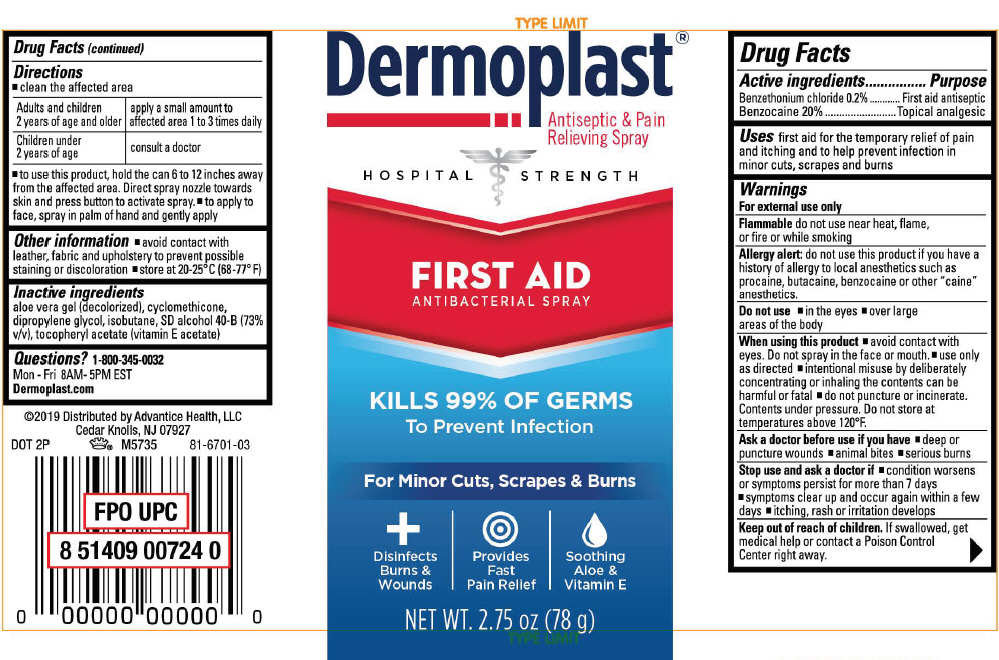 DRUG LABEL: Dermoplast First Aid
NDC: 16864-670 | Form: SPRAY
Manufacturer: Advantice Health, LLC
Category: otc | Type: HUMAN OTC DRUG LABEL
Date: 20260113

ACTIVE INGREDIENTS: BENZETHONIUM CHLORIDE 2 mg/1 g; BENZOCAINE 200 mg/1 g
INACTIVE INGREDIENTS: ALCOHOL; DIPROPYLENE GLYCOL; CYCLOMETHICONE; ALOE VERA LEAF; .ALPHA.-TOCOPHEROL ACETATE; ISOBUTANE

Dermoplast®First Aid

Drug Facts

ACTIVE INGREDIENT

PURPOSE

Active ingredients | Purposes
Benzethonium chloride 0.2% | First aid antiseptic
Benzocaine 20% | Topical analgesic

Uses

first aid for the temporary relief of pain and itching and to help prevent infection in minor cuts, scrapes and burns

Warnings

For external use only

Flammabledo not use near heat, flame, or fire or while smoking

Allergy alert:do not use this product if you have a history of allergy to local anesthetics such as procaine, butacaine, benzocaine or other "caine" anesthetics.

Do not use

- in the eyes
- over large areas of the body

When using this product

- avoid contact with eyes. Do not spray in the face or mouth.
- use only as directed
- intentional misuse by deliberately concentrating or inhaling the contents can be harmful or fatal
- do not puncture or incinerate. Contents under pressure. Do not store at temperatures above 120°F.

Ask a doctor before use if you have

- deep or puncture wounds
- animal bites
- serious burns

Stop use and ask a doctor if

- condition worsens or symptoms persist for more than 7 days
- symptoms clear up and occur again within a few days
- itching, rash or irritation develops

Keep out of reach of children.If swallowed, get medical help or contact a Poison Control Center right away.

Directions

- clean the affected area

Adults and children 2 years of age and older | apply a small amount to affected area 1 to 3 times daily
Children under 2 years of age | consult a doctor

- to use this product, hold the can 6 to 12 inches away from the affected area. Direct spray nozzle towards skin and press button to activate spray.
- to apply to face, spray in palm of hand and gently apply

Other information

- avoid contact with leather, fabric and upholstery to prevent possible staining or discoloration
- store at 20-25°C (68-77° F)

Inactive ingredients

aloe vera gel (decolorized), cyclomethicone, dipropylene glycol, isobutane, SD alcohol 40-B (73% v/v), tocopheryl acetate (vitamin E acetate)

Questions?

1-800-345-0032
Mon - Fri 8AM- 5PM EST
Dermoplast.com

Distributed by Advantice Health, LLC
Cedar Knolls, NJ 07927

PRINCIPAL DISPLAY PANEL - 78 g Can Label

Dermoplast®
Antiseptic & Pain
Relieving Spray

HOSPITAL STRENGTH

FIRST AID
ANTIBACTERIAL SPRAY

KILLS 99% OF GERMS
To Prevent Infection

For Minor Cuts, Scrapes & Burns

Disinfects
Burns &
Wounds

Provides
Fast
Pain Relief

Soothing
Aloe &
Vitamin E

NET WT. 2.75 oz (78 g)